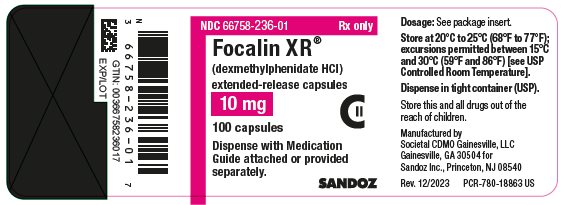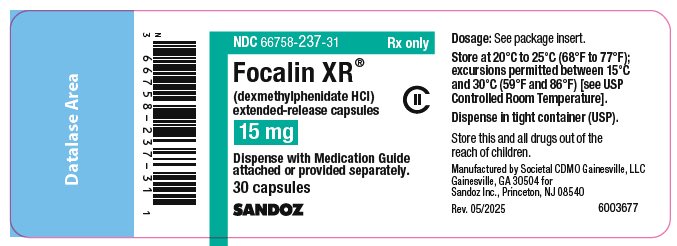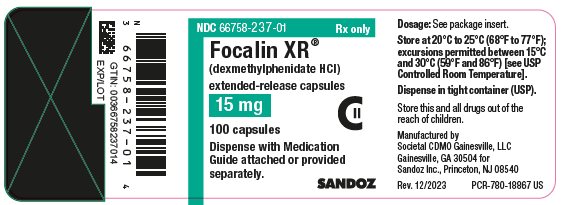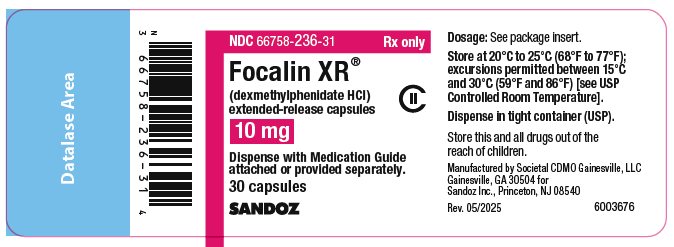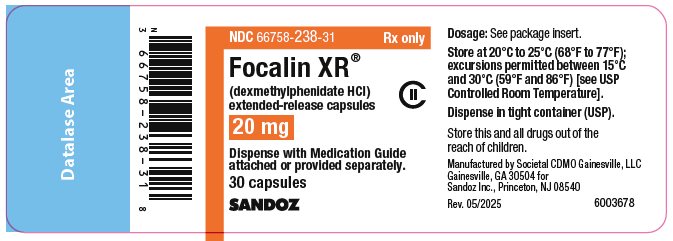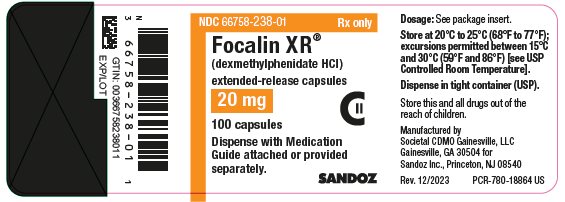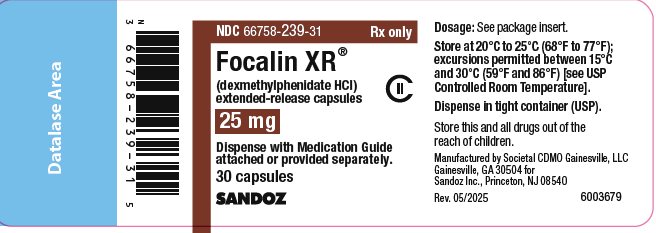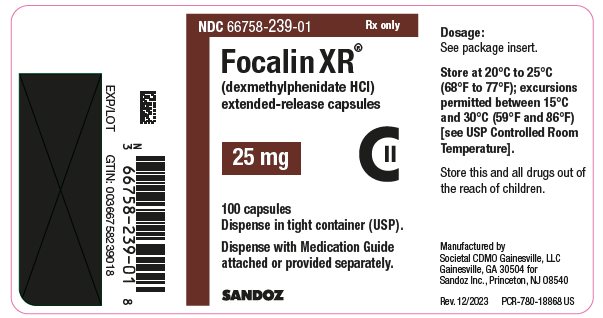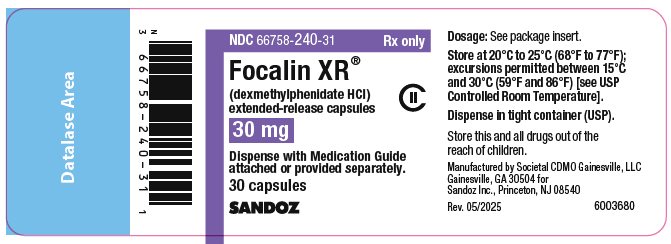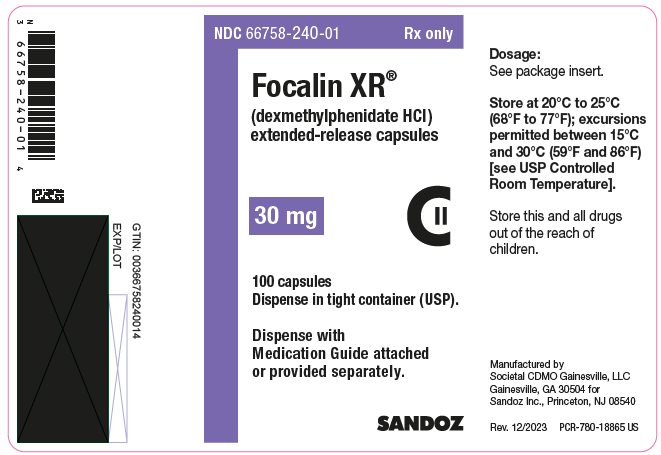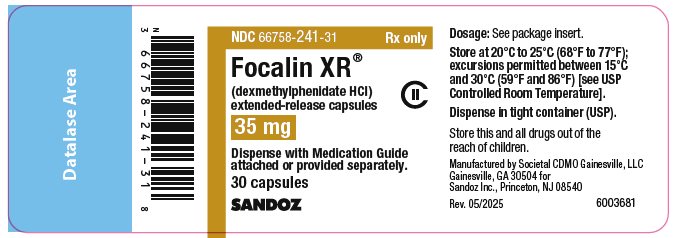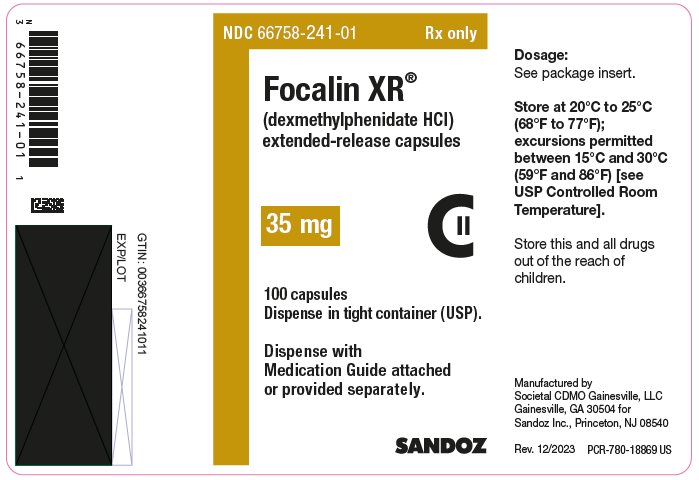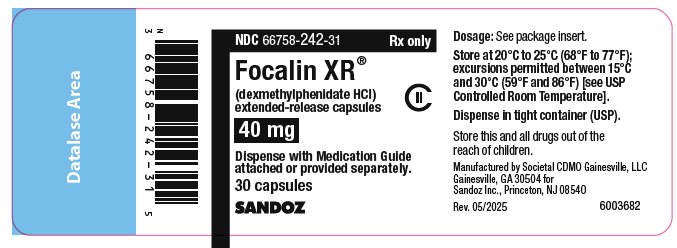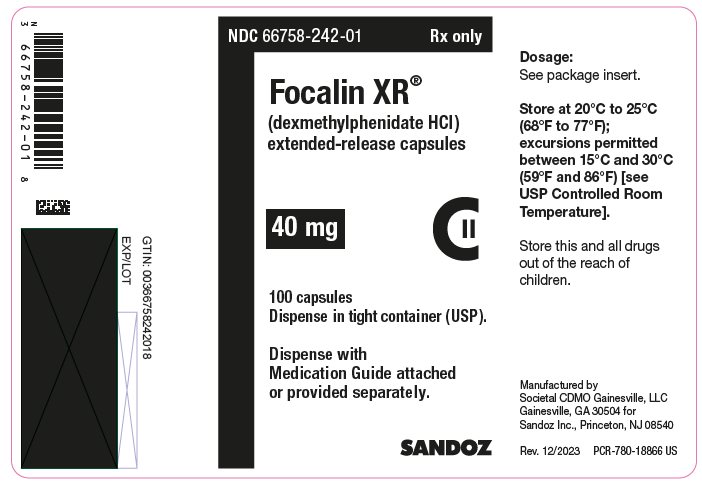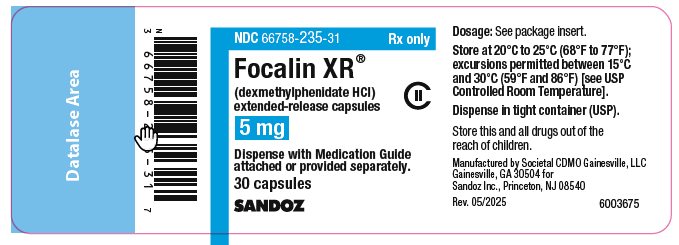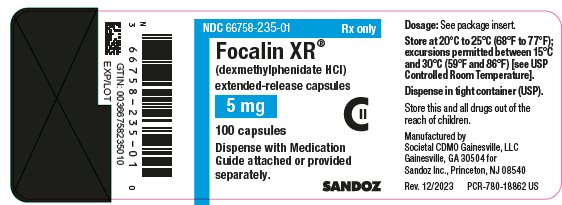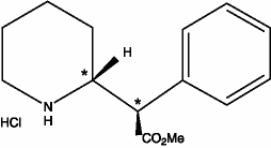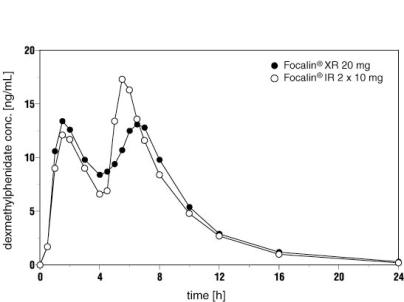 DRUG LABEL: Focalin
NDC: 66758-240 | Form: CAPSULE, EXTENDED RELEASE
Manufacturer: Sandoz Inc
Category: prescription | Type: HUMAN PRESCRIPTION DRUG LABEL
Date: 20250923
DEA Schedule: CII

ACTIVE INGREDIENTS: DEXMETHYLPHENIDATE HYDROCHLORIDE 30 mg/1 1
INACTIVE INGREDIENTS: FERRIC OXIDE YELLOW; GELATIN, UNSPECIFIED; POLYETHYLENE GLYCOL, UNSPECIFIED; DEXTROSE, UNSPECIFIED FORM; TALC; TITANIUM DIOXIDE; TRIETHYL CITRATE

HIGHLIGHTS OF PRESCRIBING INFORMATION

These highlights do not include all the information needed to use FOCALIN XR safely and effectively. See full prescribing information for FOCALIN XR.
FOCALIN XR (dexmethylphenidate hydrochloride) extended-release capsules, for oral use, CII
Initial U.S. Approval: 2005

RECENT MAJOR CHANGES

Indications and Usage (1) 09/2025

Warnings and Precautions (5.7) 09/2025

WARNING: ABUSE, MISUSE, AND ADDICTION

See full prescribing information for complete boxed warning.

Focalin XR has a high potential for abuse and misuse, which can lead to the development of a substance use disorder, including addiction. Misuse and abuse of CNS stimulants, including Focalin XR, can result in overdose and death (5.1, 9.2, 10).

- Before prescribing Focalin XR, assess each patient’s risk for abuse, misuse, and addiction.
- Educate patients and their families about these risks, proper storage of the drug, and proper disposal of any unused drug.
- Throughout treatment, reassess each patient’s risk and frequently monitor for signs and symptoms of abuse, misuse, and addiction.

1 INDICATIONS AND USAGE

Focalin XR is a central nervous system (CNS) stimulant indicated for the treatment of Attention Deficit Hyperactivity Disorder (ADHD) (1).

Limitations of Use

The use of Focalin XR is not recommended in pediatric patients younger than 6 years of age because they had higher plasma exposure and a higher incidence of adverse reactions (e.g., weight loss) than patients 6 years and older at the same dosage (5.7, 8.4).

2 DOSAGE AND ADMINISTRATION

- Patients new to methylphenidate: Recommended starting dose is 5 mg once daily for pediatric patients and 10 mg once daily for adults with or without food in the morning (2.2).
- Patients currently on methylphenidate: Focalin XR dosage is half (1/2) the current total daily dosage of methylphenidate (2.2).
- Patients currently on Focalin (dexmethylphenidate) immediate-release tablets: Give the same daily dose of Focalin XR (2.2).
- Titrate weekly in increments of 5 mg in pediatric patients and 10 mg in adult patients (2.2).
- Maximum recommended daily dose: 30 mg in pediatric patients and 40 mg in adults (2.2).
- Capsules may be swallowed whole or opened and the entire contents sprinkled on applesauce (2.3).

3 DOSAGE FORMS AND STRENGTHS

Extended-release capsules: 5 mg, 10 mg, 15 mg, 20 mg, 25 mg, 30 mg, 35 mg, and 40 mg of dexmethylphenidate hydrochloride (3).

4 CONTRAINDICATIONS

- Known hypersensitivity to methylphenidate or other components of Focalin XR (4).
- Concurrent treatment with a monoamine oxidase inhibitor (MAOI), or use of an MAOI within the preceding 14 days (4).

5 WARNINGS AND PRECAUTIONS

- Risks to Patients with Serious Cardiac Disease: Avoid use in patients with known structural cardiac abnormalities, cardiomyopathy, serious cardiac arrhythmias, coronary artery disease, or other serious cardiac disease (5.2).
- Increased Blood Pressure and Heart Rate: Monitor blood pressure and pulse (5.3).
- Psychiatric Adverse Reactions: Prior to initiating Focalin XR, screen patients for risk factors for developing a manic episode. If new psychotic or manic symptoms occur, consider discontinuing Focalin XR (5.4).
- Priapism: If abnormally sustained or frequent and painful erections occur, patients should seek immediate medical attention (5.5).
- Peripheral Vasculopathy, including Raynaud’s Phenomenon: Careful observation for digital changes is necessary during Focalin XR treatment. Further clinical evaluation (e.g., rheumatology referral) may be appropriate for patients who develop signs or symptoms of peripheral vasculopathy (5.6).
- Long-Term Suppression of Growth in Pediatric Patients: Closely monitor growth (height and weight) in pediatric patients. Pediatric patients not growing or gaining height or weight as expected may need to have their treatment interrupted (5.7).
- Acute Angle Closure Glaucoma: Focalin XR-treated patients considered at risk for acute angle closure glaucoma (e.g., patients with significant hyperopia) should be evaluated by an ophthalmologist (5.8).
- Increased Intraocular Pressure (IOP) and Glaucoma: Prescribe Focalin XR to patients with open-angle glaucoma or abnormally increased IOP only if the benefit of treatment is considered to outweigh the risk. Closely monitor patients with a history of increased IOP or open angle glaucoma (5.9).
- Motor and Verbal Tics, and Worsening of Tourette’s Syndrome: Before initiating Focalin XR, assess the family history and clinically evaluate patients for tics or Tourette’s syndrome. Regularly monitor patients for the emergence or worsening of tics or Tourette’s syndrome. Discontinue treatment if clinically appropriate (5.10).

6 ADVERSE REACTIONS

The most common adverse reactions (greater than or equal to 5% and twice the rate of placebo):

- Pediatric patients 6 to 17 years: dyspepsia, decreased appetite, headache, and anxiety (6.1).
- Adults: dry mouth, dyspepsia, headache, pharyngolaryngeal pain, and anxiety (6.1).

To report SUSPECTED ADVERSE REACTIONS, contact Sandoz Inc., at 1-800-525-8747, or FDA at 1-800-FDA-1088 or www.fda.gov/medwatch.

7 DRUG INTERACTIONS

- Antihypertensive Drugs: Monitor blood pressure. Adjust dosage of antihypertensive drug as needed (7.1).

FULL PRESCRIBING INFORMATION

WARNING: ABUSE, MISUSE, AND ADDICTION

Focalin XR has a high potential for abuse and misuse, which can lead to the development of a substance use disorder, including addiction. Misuse and abuse of CNS stimulants, including Focalin XR, can result in overdose and death [see Overdosage (10)], and this risk is increased with higher doses or unapproved methods of administration, such as snorting or injection.

Before prescribing Focalin XR, assess each patient’s risk for abuse, misuse, and addiction. Educate patients and their families about these risks, proper storage of the drug, and proper disposal of any unused drug. Throughout Focalin XR treatment, reassess each patient’s risk of abuse, misuse, and addiction and frequently monitor for signs and symptoms of abuse, misuse, and addiction [see Warnings and Precautions (5.1), Drug Abuse and Dependence (9.2)].

1 INDICATIONS AND USAGE

Focalin XR is indicated for the treatment of Attention Deficit Hyperactivity Disorder (ADHD) [see Clinical Studies (14)].

Limitations of Use

The use of Focalin XR is not recommended in pediatric patients younger than 6 years of age because they had higher plasma exposure and a higher incidence of adverse reactions (e.g., weight loss) than patients 6 years and older at the same dosage [see Warnings and Precautions (5.7), Use in Specific Populations (8.4)].

2 DOSAGE AND ADMINISTRATION

2.1 Pretreatment Screening

Prior to treating patients with Focalin XR, assess:

- for the presence of cardiac disease (i.e., perform a careful history, family history of sudden death or ventricular arrhythmia, and physical exam) [see Warnings and Precautions (5.2)].
- the family history and clinically evaluate patients for motor or verbal tics or Tourette’s syndrome before initiating Focalin XR [see Warnings and Precautions (5.10)].

2.2 Recommended Dosage

Patients New to Methylphenidate

The recommended starting dosage of Focalin XR for patients who are not currently taking dexmethylphenidate or racemic methylphenidate, or for patients who are on stimulants other than methylphenidate are:

- Pediatric patients: Start with 5 mg orally once daily in the morning with or without food.
- Adult patients: Start with 10 mg orally once daily in the morning with or without food.

Patients Currently on Methylphenidate

The recommended starting dose of Focalin XR for patients currently using methylphenidate is half (1/2) the total daily dose of racemic methylphenidate.

Patients currently using Focalin (dexmethylphenidate) immediate-release tablets may be given the same daily dose of Focalin XR.

Titration Schedule

The dose may be titrated weekly in increments of 5 mg in pediatric patients and 10 mg in adult patients. The dose should be individualized according to the needs and response of the patient. Daily doses above 30 mg in pediatrics and 40 mg in adults have not been studied and are not recommended.

2.3 Administration Instructions

Focalin XR is administered orally and may be taken whole or the capsule may be opened and the entire contents sprinkled onto applesauce. If the patient is using the sprinkled administration method, the sprinkled applesauce should be consumed immediately; it should not be stored. Patients should take the applesauce with sprinkled beads in its entirety without chewing. The dose of a single capsule should not be divided. The contents of the entire capsule should be taken, and patients should not take anything less than one capsule per day.

2.4 Dosage Reduction and Discontinuation

If paradoxical aggravation of symptoms or other adverse reactions occur, reduce the dosage, or if necessary, discontinue Focalin XR. If improvement is not observed after appropriate dosage adjustment over a one-month period, the drug should be discontinued.

3 DOSAGE FORMS AND STRENGTHS

- 5 mg extended-release capsules – light blue opaque cap and body (imprinted with “SDZ” on cap and “D5” on the body)
- 10 mg extended-release capsules – light caramel opaque cap and body (imprinted with “SDZ” on cap and “D10” on the body)
- 15 mg extended-release capsules – green opaque cap and body (imprinted with “SDZ” on cap and “D15” on the body)
- 20 mg extended-release capsules – white opaque cap and body (imprinted with “SDZ” on cap and “D20” on the body)
- 25 mg extended-release capsules – light blue opaque cap and white opaque body (imprinted with “SDZ” on cap and “D25” on the body)
- 30 mg extended-release capsules – light caramel opaque cap and white opaque body (imprinted with “SDZ” on cap and “D30” on the body)
- 35 mg extended-release capsules – light blue opaque cap and light caramel opaque body (imprinted with “SDZ” on cap and “D35” on the body)
- 40 mg extended-release capsules – green opaque cap and white opaque body (imprinted with “SDZ” on cap and “D40” on the body)

4 CONTRAINDICATIONS

- Hypersensitivity to methylphenidate or other components of Focalin XR. Hypersensitivity reactions, such as angioedema and anaphylactic reactions have been reported in patients treated with methylphenidate [see Adverse Reactions (6.1)].
- Concomitant treatment with monoamine oxidase inhibitors (MAOIs) or within 14 days following discontinuation of treatment with an MAOI, because of the risk of hypertensive crises [see Drug Interactions (7.1)].

5 WARNINGS AND PRECAUTIONS

5.1 Abuse, Misuse, and Addiction

Focalin XR has a high potential for abuse and misuse. The use of Focalin XR exposes individuals to the risks of abuse and misuse, which can lead to the development of a substance use disorder, including addiction. Focalin XR can be diverted for non-medical use into illicit channels or distribution [see Drug Abuse and Dependence (9.2)]. Misuse and abuse of CNS stimulants, including Focalin XR, can result in overdose and death [see Overdosage (10)], and this risk is increased with higher doses or unapproved methods of administration, such as snorting or injection.

Before prescribing Focalin XR, assess each patient’s risk for abuse, misuse, and addiction. Educate patients and their families about these risks and proper disposal of any unused drug. Advise patients to store Focalin XR in a safe place, preferably locked, and instruct patients to not give Focalin XR to anyone else. Throughout Focalin XR treatment, reassess each patient’s risk of abuse, misuse, and addiction and frequently monitor for signs and symptoms of abuse, misuse, and addiction.

5.2 Risks to Patients with Serious Cardiac Disease

Sudden death has been reported in patients with structural cardiac abnormalities or other serious cardiac disease who were treated with CNS stimulants at the recommended ADHD dosage.

Avoid Focalin XR use in patients with known structural cardiac abnormalities, cardiomyopathy, serious cardiac arrhythmia, coronary artery disease, or other serious cardiac disease.

5.3 Increased Blood Pressure and Heart Rate

CNS stimulants cause an increase in blood pressure (mean increase approximately 2 to 4 mmHg) and heart rate (mean increase approximately 3 to 6 beats per minute). Some patients may have larger increases.

Monitor all Focalin XR-treated patients for hypertension and tachycardia.

5.4 Psychiatric Adverse Reactions

Exacerbation of Pre-existing Psychosis

CNS stimulants may exacerbate symptoms of behavior disturbance and thought disorder in patients with a pre-existing psychotic disorder.

Induction of a Manic Episode in Patients with Bipolar Disorder

CNS stimulants may induce a manic or mixed mood episode in patients. Prior to initiating Focalin XR treatment, screen patients for risk factors for developing manic episode (e.g., comorbid or history of depressive symptoms or a family history of suicide, bipolar disorder, or depression).

New Psychotic or Manic Symptoms

CNS stimulants, at the recommended dosage, may cause psychotic or manic symptoms (e.g., hallucinations, delusional thinking, or mania) in patients without a prior history of psychotic illness or mania. In a pooled analysis of multiple short-term, placebo-controlled studies of CNS stimulants, psychotic or manic symptoms occurred in approximately 0.1% of CNS stimulant-treated patients, compared to 0% of placebo-treated patients. If such symptoms occur, consider discontinuing Focalin XR.

5.5 Priapism

Prolonged and painful erections, sometimes requiring surgical intervention, have been reported with methylphenidate use in both adult and pediatric male patients. Although priapism was not reported with methylphenidate initiation, it developed after some time on methylphenidate, often subsequent to an increase in dosage. Priapism also occurred during methylphenidate withdrawal (drug holidays or during discontinuation).

Focalin XR-treated patients who develop abnormally sustained or frequent and painful erections should seek immediate medical attention.

5.6 Peripheral Vasculopathy, Including Raynaud’s Phenomenon

CNS stimulants, including Focalin XR, used to treat ADHD are associated with peripheral vasculopathy, including Raynaud’s phenomenon. Signs and symptoms are usually intermittent and mild; however, sequelae have included digital ulceration and/or soft tissue breakdown. Effects of peripheral vasculopathy, including Raynaud’s phenomenon, were observed in post-marketing reports at and at the therapeutic dosage of CNS stimulants in all age groups throughout the course of treatment. Signs and symptoms generally improved after dosage reduction or discontinuation of the CNS stimulant.

Careful observation for digital changes is necessary during Focalin XR treatment. Further clinical evaluation (e.g., rheumatology referral) may be appropriate for Focalin XR-treated patients who develop signs or symptoms of peripheral vasculopathy.

5.7 Long-Term Suppression of Growth in Pediatric Patients

Focalin XR is not approved for use and is not recommended in pediatric patients below 6 years of age [see Use in Specific Populations (8.4)].

CNS stimulants have been associated with weight loss and slowing of growth rate in pediatric patients.

In a 7-week, double-blind, placebo-controlled study of Focalin XR, the mean weight gain was greater for pediatric patients (ages 6 to 17 years) receiving placebo (+ 0.4 kg) than for patients receiving Focalin XR (- 0.5 kg).

Careful follow-up of weight and height in pediatric patients ages 7 to 10 years who were randomized to either methylphenidate or non-medication treatment groups over 14 months, as well as in naturalistic subgroups of newly methylphenidate-treated and non-medication treated patients over 36 months (to the ages of 10 to 13 years), suggests that pediatric patients who received methylphenidate for 7 days per week throughout the year had a temporary slowing in growth rate (on average, a total of about 2 cm less growth in height and 2.7 kg less growth in weight over 3 years), without evidence of growth rebound during this development period.

Closely monitor growth (weight and height) in Focalin XR-treated pediatric patients. Pediatric patients who are not growing or gaining height or weight as expected may need to have their treatment interrupted.

5.8 Acute Angle Closure Glaucoma

There have been reports of angle closure glaucoma associated with methylphenidate treatment. Although the mechanism is not clear, Focalin XR-treated patients considered at risk for acute angle closure glaucoma (e.g., patients with significant hyperopia) should be evaluated by an ophthalmologist.

5.9 Increased Intraocular Pressure and Glaucoma

There have been reports of an elevation of intraocular pressure (IOP) associated with methylphenidate treatment [see Adverse Reactions (6.2)].

Prescribe Focalin to patients with open-angle glaucoma or abnormally increased IOP only if the benefit of treatment is considered to outweigh the risk. Closely monitor Focalin XR-treated patients with a history of abnormally increased IOP or open angle glaucoma.

5.10 Motor and Verbal Tics, and Worsening of Tourette’s Syndrome

CNS stimulants, including methylphenidate, have been associated with the onset or exacerbation of motor and verbal tics. Worsening of Tourette’s syndrome has also been reported [see Adverse Reactions (6.2)].

Before initiating Focalin XR, assess the family history and clinically evaluate patients for tics or Tourette’s syndrome. Regularly monitor Focalin -treated patients for the emergence or worsening of tics or Tourette’s syndrome, and discontinue treatment if clinically appropriate.

6 ADVERSE REACTIONS

The following are discussed in more detail in other sections of the labeling:

- Abuse, Misuse, and Addiction [see Boxed Warning, Warnings and Precautions (5.1), Drug Abuse and Dependence (9.2, 9.3)]
- Known hypersensitivity to methylphenidate or other ingredients of Focalin XR [see Contraindications (4)]
- Hypertensive Crisis with Concomitant Use of Monoamine Oxidase Inhibitors [see Contraindications (4), Drug Interactions (7.1)]
- Risks to Patients with Serious Cardiac Disease [see Warnings and Precautions (5.2)]
- Increased Blood Pressure and Heart Rate [see Warnings and Precautions (5.3)]
- Psychiatric Adverse Reactions [see Warnings and Precautions (5.4)]
- Priapism [see Warnings and Precautions (5.5)]
- Peripheral Vasculopathy, Including Raynaud’s Phenomenon [see Warnings and Precautions (5.6)]
- Long-Term Suppression of Growth in Pediatric Patients [see Warnings and Precautions (5.7)]
- Acute Angle Closure Glaucoma [see Warnings and Precautions (5.8)]
- Increased Intraocular Pressure and Glaucoma [see Warnings and Precautions (5.9)]
- Motor and Verbal Tics, and Worsening of Tourette’s Syndrome [see Warnings and Precautions (5.10)]

6.1 Clinical Trials Experience

Because clinical trials are conducted under widely varying conditions, adverse reaction rates observed in the clinical trials of a drug cannot be directly compared to rates in the clinical trials of another drug and may not reflect the rates observed in clinical practice.

Adverse Reactions in Studies with Focalin XR in Pediatric Patients with ADHD

The safety data in this section is based on data from a 7-week controlled clinical study of Focalin XR in 100 (103 randomized) pediatric patients with ADHD ages 6 to 17 years (ages 6 to 12, n = 86; ages 13 to 17, n = 17).

This study was a randomized, double-blind, placebo-controlled, parallel-group study to evaluate the time of onset, duration of efficacy, tolerability, safety of Focalin XR 5 mg to 30 mg/day who met The Diagnostic and Statistical Manual of Mental Disorders, Fourth Edition (DSM-IV) criteria for ADHD [see Clinical Studies (14.1)].

Most Common Adverse Reactions (incidence of greater than or equal to 5% and at least twice placebo): dyspepsia, decreased appetite, headache, and anxiety.

Adverse Reactions Leading to Discontinuation: 50 of 684 (7.3%) pediatric patients treated with Focalin (dexmethylphenidate) immediate-release tablets experienced an adverse reaction that resulted in discontinuation. The most common reasons for discontinuation were twitching (described as motor or vocal tics), anorexia, insomnia, and tachycardia (approximately 1% each).

Table 1 enumerates adverse reactions for the placebo-controlled, parallel-group study in children and adolescents with ADHD at flexible Focalin XR doses of 5–30 mg/day. The table includes only those events that occurred in 5% or more of patients treated with Focalin XR and for which the incidence in patients treated with Focalin XR was at least twice the incidence in placebo-treated patients.

Table 1: Common Adverse Reactions in Pediatric Patients (6 to 17 years of age) With ADHD
System organ class Adverse reaction | Focalin XR N = 53 | Placebo N = 47
Gastrointestinal disorders | 38% | 19%
Dyspepsia | 8% | 4%
Metabolism and nutrition disorders | 34% | 11%
Decreased appetite | 30% | 9%
Nervous system disorders | 30% | 13%
Headache | 25% | 11%
Psychiatric disorders | 26% | 15%
Anxiety | 6% | 0%
Abbreviation: ADHD, attention deficit hyperactivity disorder.

Table 2 below enumerates the incidence of dose-related adverse reactions that occurred during a fixed-dose, double-blind, placebo-controlled trial in pediatric patients with ADHD taking Focalin XR up to 30 mg daily versus placebo. The table includes only those reactions that occurred in patients treated with Focalin XR for which the incidence was at least 5% and greater than the incidence among placebo-treated patients.

Table 2: Dose-Related Adverse Reactions in Pediatric Patients (6 to 17 years of age) With ADHD
System organ class Adverse reaction | Focalin XR 10 mg/day N = 64 | Focalin XR 20 mg/day N = 60 | Focalin XR 30 mg/day N = 58 | Placebo N = 63
Gastrointestinal disorders | 22% | 23% | 29% | 24%
Vomiting | 2% | 8% | 9% | 0%
Metabolism and nutritional disorders | 16% | 17% | 22% | 5%
Anorexia | 5% | 5% | 7% | 0
Psychiatric disorders | 19% | 20% | 38% | 8%
Insomnia | 5% | 8% | 17% | 3%
Depression | 0 | 0 | 3% | 0
Mood swings | 0% | 0% | 3% | 2%
Other adverse reactions
Irritability | 0% | 2% | 5% | 0%
Nasal congestion | 0% | 0% | 5% | 0%
Pruritus | 0% | 0% | 3% | 0%
Abbreviation: ADHD, attention deficit hyperactivity disorder.

Adverse Reactions in Studies with Focalin XR in Adult Patients with ADHD

The safety data in this section is based on data from a 5-week controlled clinical study of Focalin XR in 218 adult patients (221 randomized) with ADHD ages 18 to 60 years. In this study, 101 adult patients were treated for at least 6 months.

This study was a randomized, double-blind, placebo-controlled, parallel-group study to evaluate the efficacy, safety, and tolerability of Focalin XR 20 mg, 30 mg, or 40 mg daily who met DSM-IV criteria for ADHD [see Clinical Studies (14.2)].

Most Common Adverse Reactions (incidence of greater than or equal to 5% and at least twice placebo): dry mouth, dyspepsia, headache, anxiety, and pharyngolaryngeal pain.

Adverse Reactions Leading to Discontinuation: During the double-blind phase of the study, 10.7% of the Focalin XR-treated patients and 7.5% of the placebo-treated patients discontinued due to adverse reactions. Three patients (1.8%) in the Focalin XR discontinued due to insomnia and jittery respectively; and two patients (1.2%) in the Focalin XR discontinued due to anorexia and anxiety, respectively.

Table 3 enumerates adverse reactions for the placebo-controlled, parallel-group study in adults with ADHD at fixed Focalin XR doses of 20, 30, or 40 mg/day. The table includes only those events that occurred in 5% or more of patients in a Focalin XR dose group and for which the incidences in patients treated with Focalin XR appeared to increase with dose.

Table 3: Dose-Related Adverse Reactions in Adult Patients (18 to 60 years of age) With ADHD
System organ class Adverse reaction | Focalin XR 20 mg N = 57 | Focalin XR 30 mg N = 54 | Focalin XR 40 mg N = 54 | Placebo N = 53
Gastrointestinal disorders | 28% | 32% | 44% | 19%
Dry mouth | 7% | 20% | 20% | 4%
Dyspepsia | 5% | 9% | 9% | 2%
Nervous system disorders | 37% | 39% | 50% | 28%
Headache | 26% | 30% | 39% | 19%
Psychiatric disorders | 40% | 43% | 46% | 30%
Anxiety | 5% | 11% | 11% | 2%
Respiratory, thoracic, and mediastinal disorders | 16% | 9% | 15% | 8%
Pharyngolaryngeal pain | 4% | 4% | 7% | 2%

Two other adverse reactions occurring in clinical trials with Focalin XR at a frequency greater than placebo, but which were not dose related were: feeling jittery (12% and 2%, respectively) and dizziness (6% and 2%, respectively).

Table 4 summarizes changes in vital signs and weight that were recorded in the adult study (N = 218) of Focalin XR in the treatment of ADHD.

Table 4: Changes (Mean ± SD) in Vital Signs and Weight by Randomized Dose During Double-Blind Treatment–Adults
 | Focalin XR 20 mg (N = 57) | Focalin XR 30 mg (N = 54) | Focalin XR 40 mg (N = 54) | Placebo (N = 53)
Pulse (bpm) | 3.1 ± 11.1 | 4.3 ± 11.7 | 6 ± 10.1 | -1.4 ± 9.3
Diastolic BP (mmHg) | -0.2 ± 8.2 | 1.2 ± 8.9 | 2.1 ± 8 | 0.3 ± 7.8
Weight (kg) | -1.4 ± 2 | -1.2 ± 1.9 | -1.7 ± 2.3 | -0.1 ± 3.9

6.2 Postmarketing Experience

The following additional adverse reactions have been identified during postapproval use of dexmethylphenidate. Because these reactions are reported voluntarily from a population of uncertain size, it is not always possible to reliably estimate their frequency or establish a causal relationship to drug exposure.

Musculoskeletal: rhabdomyolysis

Immune System Disorders: hypersensitivity reactions, including angioedema and anaphylaxis

Adverse Reactions Reported With All Ritalin and Focalin Formulations

The following adverse reactions associated with the use of all Ritalin and Focalin formulations were identified in clinical trials, spontaneous reports, and literature. Because these reactions were reported voluntarily from a population of uncertain size, it is not always possible to estimate their frequency reliably or to establish a causal relationship to drug exposure.

Infections and Infestations: nasopharyngitis

Blood and the Lymphatic System Disorders: leukopenia, thrombocytopenia, anemia

Immune System Disorders: hypersensitivity reactions, including angioedema and anaphylaxis

Metabolism and Nutrition Disorders: decreased appetite, reduced weight gain, and suppression of growth during prolonged use in pediatric patients

Psychiatric Disorders: insomnia, anxiety, restlessness, agitation, psychosis (sometimes with visual and tactile hallucinations), depressed mood, depression

Nervous System Disorders: headache, dizziness, tremor, dyskinesia, including choreoathetoid movements, drowsiness, convulsions, cerebrovascular disorders (including vasculitis, cerebral hemorrhages and cerebrovascular accidents), serotonin syndrome in combination with serotonergic drugs

Eye Disorders: blurred vision, difficulties in visual accommodation

Cardiac Disorders: tachycardia, palpitations, increased blood pressure, arrhythmias, angina pectoris

Respiratory, Thoracic, and Mediastinal Disorders: cough

Gastrointestinal Disorders: dry mouth, nausea, vomiting, abdominal pain, dyspepsia

Hepatobiliary Disorders: abnormal liver function, ranging from transaminase elevation to severe hepatic injury

Skin and Subcutaneous Tissue Disorders: hyperhidrosis, pruritus, urticaria, exfoliative dermatitis, scalp hair loss, erythema multiforme rash, thrombocytopenic purpura

Musculoskeletal and Connective Tissue Disorders: arthralgia, muscle cramps, rhabdomyolysis, trismus

Investigations: weight loss (adult ADHD patients)

Vascular Disorders: peripheral coldness, Raynaud's phenomenon

Additional Adverse Reactions Reported with Other Methylphenidate Products

The list below shows adverse reactions not listed with Ritalin and Focalin formulations that have been reported with other methylphenidate products based on clinical trials data and post-marketing spontaneous reports.

Blood and Lymphatic Disorders: pancytopenia

Immune System Disorders: hypersensitivity reactions, such as auricular swelling, bullous conditions, eruptions, exanthemas

Psychiatric Disorders: affect lability, mania, disorientation, libido changes

Nervous System Disorders: migraine, motor and verbal tics

Eye Disorders: diplopia, increased intraocular pressure, mydriasis

Cardiac Disorders: sudden cardiac death, myocardial infarction, bradycardia, extrasystole, supraventricular tachycardia, ventricular extrasystole

Respiratory, Thoracic, and Mediastinal Disorders: pharyngolaryngeal pain, dyspnea

Gastrointestinal Disorders: diarrhea, constipation

Skin and Subcutaneous Tissue Disorders: angioneurotic edema, erythema, fixed drug eruption

Musculoskeletal, Connective Tissue, and Bone Disorders: myalgia, muscle twitching

Renal and Urinary Disorders: hematuria

Reproductive System and Breast Disorders: gynecomastia

General Disorders: fatigue, hyperpyrexia

Urogenital Disorders: priapism

7 DRUG INTERACTIONS

7.1 Clinically Important Drug Interactions With Focalin XR

Table 5 presents clinically important drug interactions with Focalin XR.

Table 5: Clinically Important Drug Interactions With Focalin XR
Monoamine Oxidase Inhibitors (MAOIs)
Clinical Impact | Concomitant use of MAOIs and CNS stimulants, including Focalin XR, can; cause hypertensive crisis. Potential outcomes include death, stroke,; myocardial infarction, aortic dissection, ophthalmological complications,; eclampsia, pulmonary edema, and renal failure [see Contraindications (4)].
Intervention | Concomitant use of Focalin XR with MAOIs or within 14 days after; discontinuing MAOI treatment is contraindicated.
Antihypertensive Drugs
Clinical impact | Focalin XR may decrease the effectiveness of drugs used to treat hypertension; [see Warnings and Precautions (5.3)].
Intervention | Monitor blood pressure and adjust the dosage of the antihypertensive drug as; needed.
Halogenated Anesthetics
Clinical impact | Concomitant use of halogenated anesthetics and Focalin XR may increase the; risk of sudden blood pressure and heart rate increase during surgery.
Intervention | Avoid use of Focalin XR in patients being treated with anesthetics on the day; of surgery.
Risperidone
Clinical impact | Combined use of methylphenidate with risperidone when there is a change,; whether an increase or decrease, in dosage of either or both medications, may; increase the risk of extrapyramidal symptoms (EPS)
Intervention | Monitor for signs of EPS

8 USE IN SPECIFIC POPULATIONS

8.1 Pregnancy

Pregnancy Exposure Registry

There is a pregnancy exposure registry that monitors pregnancy outcomes in women exposed to ADHD medications, including Focalin XR, during pregnancy. Healthcare providers are encouraged to register patients by calling the National Pregnancy Registry for ADHD medications at 1-866-961-2388 or visiting https://womensmentalhealth.org/adhd-medications/.

Risk Summary

Dexmethylphenidate is the d-threo enantiomer of racemic methylphenidate. Published studies and postmarketing reports on methylphenidate use during pregnancy have not identified a drug-associated risk of major birth defects, miscarriage or adverse maternal or fetal outcomes. There may be risks to the fetus associated with the use of CNS stimulants during pregnancy (see Clinical Considerations). Embryo-fetal development studies in rats showed delayed fetal skeletal ossification at doses up to 5 times the maximum recommended human dose (MRHD) of 20 mg/day given to adults based on plasma levels. A decrease in pup weight in males was observed in a pre- and post-natal development study with oral administration of methylphenidate to rats throughout pregnancy and lactation at doses 5 times the MRHD of 20 mg/day given to adults based on plasma levels (see Data).

The estimated background risk of major birth defects and miscarriage for the indicated population is unknown. All pregnancies have a background risk of birth defect, loss, or other adverse outcomes. In the U.S. general population, the estimated background risk of major birth defects and miscarriage in clinically recognized pregnancies is 2% to 4% and 15% to 20%, respectively.

Clinical Considerations

Fetal/Neonatal Adverse Reactions

CNS stimulants, such as Focalin XR, can cause vasoconstriction and thereby decrease placental perfusion. No fetal and/or neonatal adverse reactions have been reported with the use of therapeutic doses of methylphenidate during pregnancy; however, premature delivery and low birth weight infants have been reported in amphetamine-dependent mothers.

Data

Animal Data

In embryo-fetal development studies conducted in rats and rabbits, dexmethylphenidate was administered orally at doses of up to 20 and 100 mg/kg/day, respectively, during the period of organogenesis. No evidence of malformations was found in either the rat or rabbit study; however, delayed fetal skeletal ossification was observed at the highest dose level in rats. When dexmethylphenidate was administered to rats throughout pregnancy and lactation at doses of up to 20 mg/kg/day, post-weaning body weight gain was decreased in male offspring at the highest dose, but no other effects on postnatal development were observed. At the highest doses tested, plasma levels [area under the curves (AUCs)] of dexmethylphenidate in pregnant rats and rabbits were approximately 5 and 1 times, respectively, those in adults dosed with 20 mg/day. Plasma levels in adults were comparatively similar to plasma levels in adolescents.

Racemic methylphenidate has been shown to cause malformations (increased incidence of fetal spina bifida) in rabbits when given in doses of 200 mg/kg/day throughout organogenesis.

8.2 Lactation

Risk Summary

Dexmethylphenidate is the d-threo enantiomer of racemic methylphenidate. Limited published literature, based on milk sampling from seven mothers’ reports that methylphenidate is present in human milk, which resulted in infant doses of 0.16% to 0.7% of the maternal weight-adjusted dosage and a milk/plasma ratio ranging between 1.1 and 2.7. There are no reports of adverse effects on the breastfed infant and no effects on milk production. Long-term neurodevelopmental effects on infants from stimulant exposure are unknown. The developmental and health benefits of breastfeeding should be considered along with the mother’s clinical need for Focalin XR and any potential adverse effects on the breastfed infant from Focalin XR or from the underlying maternal condition.

Clinical Considerations

Monitor breastfeeding infants for adverse reactions, such as agitation, insomnia, anorexia, and reduced weight gain.

8.4 Pediatric Use

The safety and effectiveness of Focalin XR have not been established in pediatric patients below the age of 6 years.

In studies evaluating extended-release methylphenidate products, patients 4 to <6 years of age had higher systemic methylphenidate exposures than those observed in older pediatric patients at the same dosage. Pediatric patients 4 to <6 years of age also had a higher incidence of adverse reactions, including weight loss.

The safety and effectiveness of Focalin XR for the treatment of ADHD have been established in pediatric patients aged 6 to 17 years in two adequate and well-controlled clinical trials [see Clinical Studies (14.2)].

Long Term Suppression of Growth

Growth should be monitored during treatment with stimulants, including Focalin XR. Pediatric patients who are not growing or gaining weight as expected may need to have their treatment interrupted [see Warnings and Precautions (5.7)].

Juvenile Animal Toxicity Data

Rats treated with racemic methylphenidate early in the postnatal period through sexual maturation demonstrated a decrease in spontaneous locomotor activity in adulthood. A deficit in acquisition of a specific learning task was observed in females only. The doses at which these findings were observed are at least 6 times the MRHD of 60 mg/day given to children on a mg/m^2 basis.

In a study conducted in young rats, racemic methylphenidate was administered orally at doses of up to 100 mg/kg/day for 9 weeks, starting early in the postnatal period (postnatal Day 7) and continuing through sexual maturity (postnatal Week 10). When these animals were tested as adults (postnatal Weeks 13 to 14), decreased spontaneous locomotor activity was observed in males and females previously treated with 50 mg/kg/day (approximately 4 times the MRHD of 60 mg/day of racemic methylphenidate given to children on a mg/m^2 basis) or greater, and a deficit in the acquisition of a specific learning task was seen in females exposed to the highest dose (8 times the MRHD given to children on a mg/m^2 basis). The no effect level for juvenile neurobehavioral development in rats was 5 mg/kg/day (approximately 0.5 times the MRHD given to children on a mg/m^2 basis). The clinical significance of the long-term behavioral effects observed in rats is unknown.

8.5 Geriatric Use

Focalin XR has not been studied in the geriatric population.

9 DRUG ABUSE AND DEPENDENCE

9.1 Controlled Substance

Focalin XR contains dexmethylphenidate hydrochloride, a Schedule II controlled substance.

9.2 Abuse

Focalin XR has a high potential for abuse and misuse which can lead to the development of a substance use disorder, including addiction [see Warnings and Precautions (5.1)]. Focalin XR can be diverted for non-medical use into illicit channels or distribution.

Abuse is the intentional non-therapeutic use of a drug, even once, to achieve a desired psychological or physiological effect. Misuse is the intentional use, for therapeutic purposes, of a drug by an individual in a way other than prescribed by a health care provider or for whom it was not prescribed. Drug addiction is a cluster of behavioral, cognitive, and physiological phenomena that may include a strong desire to take the drug, difficulties in controlling drug use (e.g., continuing drug use despite harmful consequences, giving a higher priority to drug use than other activities and obligations), and possible tolerance or physical dependence.

Misuse and abuse of methylphenidate may cause increased heart rate, respiratory rate, or blood pressure; sweating; dilated pupils; hyperactivity; restlessness; insomnia; decreased appetite; loss of coordination; tremors; flushed skin; vomiting; and/or abdominal pain. Anxiety, psychosis, hostility, aggression, and suicidal or homicidal ideation have also been observed with CNS stimulants abuse and/or misuse. Misuse and abuse of CNS stimulants, including Focalin XR, can result in overdose and death [see Overdosage (10)], and this risk is increased with higher doses or unapproved methods of administration, such as snorting or injection.

9.3 Dependence

Physical Dependence

Focalin XR may produce physical dependence. Physical dependence is a state that develops as a result of physiological adaptation in response to repeated drug use, manifested by withdrawal signs and symptoms after abrupt discontinuation or a significant dose reduction of a drug.

Withdrawal signs and symptoms after abrupt discontinuation or dose reduction following prolonged use of CNS stimulants including Focalin XR include dysphoric mood; depression; fatigue; vivid, unpleasant dreams; insomnia or hypersomnia; increased appetite; and psychomotor retardation or agitation.

Tolerance

Focalin XR may produce tolerance. Tolerance is a physiological state characterized by a reduced response to a drug after repeated administration (i.e., a higher dose of a drug is required to produce the same effect that was once obtained at a lower dose).

10 OVERDOSAGE

Clinical Effects of Overdose

Overdose of CNS stimulants is characterized by the following sympathomimetic effects:

- Cardiovascular effects including tachyarrhythmias, and hypertension or hypotension. Vasospasm, myocardial infarction, or aortic dissection may precipitate sudden cardiac death. Takotsubo cardiomyopathy may develop.
- CNS effects including psychomotor agitation, confusion, and hallucinations. Serotonin syndrome, seizures, cerebral vascular accidents, and coma may occur.
- Life-threatening hyperthermia (temperatures greater than 104°F) and rhabdomyolysis may develop.

Overdose Management

Consider the possibility of multiple drug ingestion. The pharmacokinetic profile of Focalin XR should be considered when treating patients with overdose. Because methylphenidate has a large volume of distribution and is rapidly metabolized, dialysis is not useful. Consider contacting the Poison Help line (1-800-222-1222) or a medical toxicologist for additional overdose management recommendations.

11 DESCRIPTION

Focalin XR contains dexmethylphenidate hydrochloride, a CNS stimulant. Dexmethylphenidate hydrochloride is the d-threo enantiomer of racemic methylphenidate hydrochloride. Focalin XR is an extended-release formulation of dexmethylphenidate with a bi-modal release profile. Each bead-filled Focalin XR capsule contains half the dose as immediate-release beads and half as enteric-coated, delayed-release beads, thus providing an immediate release of dexmethylphenidate and a delayed release of dexmethylphenidate. Focalin XR is intended for oral administration and is available as 5 mg, 10 mg, 15 mg, 20 mg, 25 mg, 30 mg, 35 mg, and 40 mg extended-release capsules.

Chemically, dexmethylphenidate hydrochloride is methyl α-phenyl-2-piperidineacetate hydrochloride, (R,R’)-(+)-. Its molecular formula is C14H19NO2•HCl. Its structural formula is:

Note* = asymmetric carbon center

Dexmethylphenidate hydrochloride is a white to off-white powder. Its solutions are acid to litmus. It is freely soluble in water and in methanol, soluble in alcohol, and slightly soluble in chloroform and in acetone. Its molecular weight is 269.77 g/mol.

Inactive ingredients: ammonio methacrylate copolymer, gelatin, methacrylic acid copolymer, polyethylene glycol, sugar spheres, talc, titanium dioxide, and triethyl citrate.

Each strength capsule also contains colorant ingredients in the capsule shell as follows:

- 5 mg: E132 FD&C Blue No. 2
- 10 mg: FDA/E172 iron oxide yellow
- 15 mg: FD&C Blue No. 2, FDA/E172 iron oxide yellow
- 20 mg: contains no colorants
- 25 mg: E132 FD&C Blue No. 2
- 30 mg: FDA/E172 iron oxide yellow
- 35 mg: E132 FD&C Blue No. 2, FDA/E172 iron oxide yellow
- 40 mg: E132 FD&C Blue No. 2, FDA/E172 iron oxide yellow

12 CLINICAL PHARMACOLOGY

12.1 Mechanism of Action

Dexmethylphenidate hydrochloride is a CNS stimulant. The mode of therapeutic action in ADHD is not known.

12.2 Pharmacodynamics

Dexmethylphenidate is the more pharmacologically active d-enantiomer of racemic methylphenidate. Methylphenidate blocks the reuptake of norepinephrine and dopamine into the presynaptic neuron and increase the release of these monoamines into the extraneuronal space.

Cardiac Electrophysiology

At the recommended maximum total daily dosage of 40 mg, Focalin XR does not prolong the QTc interval to any clinically relevant extent.

12.3 Pharmacokinetics

Absorption

Focalin XR produces a bi-modal plasma concentration-time profile (i.e., 2 distinct peaks approximately 4 hours apart) when orally administered to healthy adults. The initial rate of absorption for Focalin XR is similar to that of Focalin tablets as shown by the similar rate parameters between the 2 formulations, i.e., first peak concentration (Cmax1), and time to the first peak (tmax1), which is reached in 1.5 hours (typical range 1 to 4 hours). The mean time to the interpeak minimum (tminip) is slightly shorter, and time to the second peak (tmax2) is slightly longer for Focalin XR given once daily (about 6.5 hours; range, 4.5 to 7 hours) compared to Focalin tablets given in 2 doses 4 hours apart (see Figure 1), although the ranges observed are greater for Focalin XR.

Focalin XR given once daily exhibits a lower second peak concentration (Cmax2), higher interpeak minimum concentrations (Cminip), and fewer peak and trough fluctuations than Focalin tablets given in 2 doses given 4 hours apart. This is due to an earlier onset and more prolonged absorption from the delayed-release beads (see Figure 1).

The ratio of geometric mean of AUC(0-inf) and Cmax after administration of Focalin XR given once daily are 1.02 and 0.86 respectively, to the same total dose of Focalin tablets given in 2 doses 4 hours apart. The variability in Cmax, Cmin, and AUC is similar between Focalin XR and Focalin immediate-release tablets with approximately a 3-fold range in each.

Approximately 90% of the dose is absorbed after oral administration of radiolabeled racemic methylphenidate. However, due to first pass metabolism the mean absolute bioavailability of dexmethylphenidate when administered in various formulations was 22% to 25%.

Figure 1. Mean Dexmethylphenidate Plasma Concentration-Time Profiles After Administration 1 x 20 mg Focalin XR (n = 24) Capsules and 2 x 10 mg Focalin Immediate-Release Tablets (n = 25)

After single dose administration, Focalin XR demonstrated dose proportional pharmacokinetics (PK) in the range of 5 mg to 40 mg.

For patients unable to swallow the capsule, the contents may be sprinkled on applesauce and administered [see Dosage and Administration (2)].

Distribution

The plasma protein binding of dexmethylphenidate is not known; racemic methylphenidate is bound to plasma proteins by 12% to 15%, independent of concentration. Dexmethylphenidate shows a volume of distribution of 2.65 ± 1.11 L/kg.

Elimination

Plasma dexmethylphenidate concentrations decline monophasically following oral administration of Focalin XR. The mean terminal elimination half-life of dexmethylphenidate was about 3 hours in healthy adults. Pediatric patients tend to have slightly shorter half-lives with means of 2 to 3 hours. Dexmethylphenidate was eliminated with a mean clearance of 0.40 ± 0.12 L/hr/kg after intravenous administration.

Metabolism

In humans, dexmethylphenidate is metabolized primarily via de-esterification to d-α-phenyl-piperidine acetic acid (also known as d-ritalinic acid). This metabolite has little or no pharmacological activity. There is no in vivo interconversion to the l-threo-enantiomer.

Excretion

After oral dosing of radiolabeled racemic methylphenidate in humans, about 90% of the radioactivity was recovered in urine. The main urinary metabolite of racemic dl- methylphenidate was dl-ritalinic acid, accountable for approximately 80% of the dose. Urinary excretion of parent compound accounted for 0.5% of an intravenous dose.

Studies in Specific Populations

Male and Female Patients

After administration of Focalin XR, the first peak, (Cmax1) was on average 45% higher in women. The interpeak minimum and the second peak also tended to be slightly higher in women although the difference was not statistically significant, and these patterns remained even after weight normalization.

Racial or Ethnic Groups

There is insufficient experience with the use of Focalin XR to detect ethnic variations in pharmacokinetics.

Pediatric Patients

The pharmacokinetics of dexmethylphenidate after Focalin XR administration have not been studied in pediatrics less than 18 years of age. When a similar formulation of racemic methylphenidate was examined in 15 patients between 10 and 12 years of age, and 3 patients with ADHD between 7 and 9 years of age, the time to the first peak was similar, although the time until the between peak minimum, and the time until the second peak were delayed and more variable in pediatric patients compared to adults. After administration of the same dose to pediatric patients and adults, concentrations in pediatric patients were approximately twice the concentrations observed in adults. This higher exposure is almost completely due to smaller body size as no relevant age-related differences in dexmethylphenidate pharmacokinetic parameters (i.e., clearance and volume of distribution) are observed after normalization to dose and weight.

Patients with Renal Impairment

There is no experience with the use of Focalin XR in patients with renal impairment. Since renal clearance is not an important route of methylphenidate elimination, renal impairment is expected to have little effect on the pharmacokinetics of Focalin XR.

Patients with Hepatic Impairment

There is no experience with the use of Focalin XR in patients with hepatic impairment.

Drug Interaction Studies

Methylphenidate is not metabolized by cytochrome P450 (CYP) isoenzymes to a clinically relevant extent. Inducers or inhibitors of CYPs are not expected to have any relevant impact on methylphenidate pharmacokinetics. Conversely, the d- and l-enantiomers of methylphenidate did not relevantly inhibit CYP1A2, 2C8, 2C9, 2C19, 2D6, 2E1, or 3A. Clinically, methylphenidate coadministration did not increase plasma concentrations of the CYP2D6 substrate desipramine.

13 NONCLINICAL TOXICOLOGY

13.1 Carcinogenesis, Mutagenesis, and Impairment of Fertility

Carcinogenesis

Lifetime carcinogenicity studies have not been carried out with dexmethylphenidate. In a lifetime carcinogenicity study carried out in B6C3F1 mice, racemic methylphenidate caused an increase in hepatocellular adenomas and, in males only, an increase in hepatoblastomas was seen at a daily dose of approximately 60 mg/kg/day. This dose is approximately 2 times the MRHD of 60 mg/day of racemic methylphenidate given to children on a mg/m^2 basis. Hepatoblastoma is a relatively rare rodent malignant tumor type. There was no increase in total malignant hepatic tumors. The mouse strain used is sensitive to the development of hepatic tumors, and the significance of these results to humans is unknown.

Racemic methylphenidate did not cause any increase in tumors in a lifetime carcinogenicity study carried out in F344 rats; the highest dose used was approximately 45 mg/kg/day, which is approximately 4 times the MRHD (children) of 60 mg/day of racemic methylphenidate in children on a mg/m^2 basis.

In a 24-week carcinogenicity study with racemic methylphenidate in the transgenic mouse strain p53+/-, which is sensitive to genotoxic carcinogens, there was no evidence of carcinogenicity. Male and female mice were fed diets containing the same concentrations as in the lifetime carcinogenicity study; the high-dose group was exposed to 60 to 74 mg/kg/day of racemic methylphenidate.

Mutagenesis

Dexmethylphenidate was not mutagenic in the in vitro Ames reverse mutation assay, in the in vitro mouse lymphoma cell forward mutation assay, or in the in vivo mouse bone marrow micronucleus test. In an in vitro assay using cultured Chinese Hamster Ovary cells treated with racemic methylphenidate, sister chromatid exchanges and chromosome aberrations were increased, indicative of a weak clastogenic response.

Impairment of Fertility

No human data on the effect of methylphenidate on fertility are available.

Fertility studies have not been conducted with dexmethylphenidate. Racemic methylphenidate did not impair fertility in male or female mice that were fed diets containing the drug in an 18-week continuous breeding study. The study was conducted at doses of up to 160 mg/kg/day, approximately 10 times the MRHD of 60 mg/day of racemic methylphenidate given to adolescents on a mg/m^2 basis.

14 CLINICAL STUDIES

14.1 Pediatric Patients

A randomized, double-blind, placebo-controlled, parallel-group study (Study 1) was conducted in 103 pediatric patients (ages 6 to 12, n = 86; ages 13 to 17, n = 17) who met DSM-IV criteria for ADHD inattentive, hyperactive-impulsive or combined inattentive/hyperactive-impulsive subtypes (Study 1).

Patients were randomized to receive either a flexible-dose of Focalin XR (5 to 30 mg/day) or placebo once daily for 7 weeks. During the first 5 weeks of treatment, patients were titrated to their optimal dose and remained on this optimal dose for the last 2 weeks of the study without dose changes or interruption.

Signs and symptoms of ADHD were evaluated by comparing the mean change from baseline to endpoint for Focalin XR and placebo-treated patients using an intent-to-treat analysis of the primary efficacy outcome measure, the DSM-IV total subscale score of the Conners ADHD/DSM-IV Scales for teachers (CADS-T). The CADS-T includes the ADHD Index (12 items) and the DSM-IV total subscale (18 items, total score range: 0 to 54); the latter is divided into inattentive (9 items) and hyperactive-impulsive (9 items) subscales. Teachers assessed behavior observed during the school day by completing the CADS-T weekly. A decrease in the CADS-T DSM-IV total subscale score from baseline indicates improvement.

The CADS-T total scores showed a statistically significant treatment effect in favor of Focalin XR than placebo (Table 6). There were insufficient adolescents enrolled in this study to assess the efficacy for Focalin XR in the adolescent population. However, pharmacokinetic considerations and evidence of effectiveness of immediate-release Focalin in adolescents support the effectiveness of Focalin XR in this population.

Table 6: Summary of Efficacy Results from ADHD Study in Pediatric Patients (6 – 17 years) (Study 1)
Study number | Treatment group | Primary efficacy measure: CADS-T total score
Study number | Treatment group | Mean baseline score (SD) | LS mean change from baseline (SE) | Placebo-subtracted differencea (95% CI)
Study 1 | Focalin XR 5-30 mg/day (n = 52) | 33.3 (9.18) | 16.41 (1.8) | 10.64 (5.38, 15.91)
 | Placebo (n = 45) | 34.9 (10.03) | 5.77 (1.93) | --
Abbreviations: ADHD, attention deficit hyperactivity disorder; SD, standard deviation; SE, standard error; LS Mean, least-squares mean; CI, confidence interval, not adjusted for multiple comparisons.
aDifference (drug minus placebo) in least-squares mean change from baseline.

In 2 additional cross-over studies (Studies 2 and 3) in pediatric patients ages 6 to 12 years, who received 20 mg Focalin XR or placebo, Focalin XR was found to have a statistically significant treatment effect versus placebo on the Swanson, Kotkin, Agler, M-Flynn & Pelham (SKAMP) rating scale total scores at all-time points after dosing in each study (0.5, 1, 3, 4, 5, 7, 9, 10, 11, and 12 hours in Study 2 and 1, 2, 4, 6, 8, 9, 10, 11, and 12 hours in the study 3). SKAMP is a validated 13-item teacher-rated scale that assesses manifestations of ADHD in a classroom setting. A treatment effect was also observed 0.5 hours after administration of Focalin XR 20 mg in an additional study of ADHD patients ages 6 to 12 years.

14.2 Adult Patients

A randomized, double-blind, placebo-controlled, parallel-group (Study 4) was conducted in 221 adult patients ages 18 to 60 years who met DSM-IV criteria for ADHD inattentive, hyperactive-impulsive or combined inattentive/hyperactive-impulsive subtypes (Study 4).

Patients were randomized to receive either a fixed dose of Focalin XR (20, 30, or 40 mg/day) or placebo once daily for 5 weeks. Patients randomized to Focalin XR were initiated on a 10 mg/day starting dose and titrated in increments of 10 mg/week to the randomly assigned fixed dose. Patients were maintained on their fixed dose (20, 30, or 40 mg/day) for a minimum of 2 weeks.

Signs and symptoms of ADHD were evaluated by comparing the mean change from baseline to endpoint for Focalin XR and placebo-treated patients using an intent-to-treat analysis of the primary efficacy outcome measure, the investigator-administered DSM-IV Attention-Deficit/Hyperactivity Disorder Rating Scale (DSM-IV ADHD-RS).

The DSM-IV ADHD-RS is an 18-item questionnaire with a score range of 0 to 54 points that measures the core symptoms of ADHD and includes both hyperactive/impulsive and inattentive subscales.

All 3 Focalin XR doses (20, 30, and 40 mg/day) showed a statistically significant treatment effect compared to placebo. There was no obvious increase in effectiveness with increasing the dose.

Table 7: Summary of Efficacy Results from ADHD Study in Adults (Study 4)
Study number | Treatment group | Primary efficacy Measure: ADHD-RS total score
Study number | Treatment group | Mean baseline score (SD) | LS mean change from baseline (SE) | Placebo-subtracted differencea (95% CI)
Study 4 | Focalin XR 20 mg/day (n = 57) | 36.8 (7.2) | 13.27 (1.44) | 5.71 (1.64, 9.78)
Study 4 | Focalin XR 30 mg/day (n = 54) | 36.9 (8.07) | 12.86 (1.48) | 5.31 (1.18, 9.44)
Study 4 | Focalin XR 40 mg/day (n = 54) | 36.9 (8.25) | 16.51 (1.48) | 8.96 (4.83, 13.08)
Study 4 | Placebo (n = 53) | 37.5 (7.82) | 7.55 (1.49) | --
Abbreviations: ADHD, attention deficit hyperactivity disorder; SD, standard deviation; SE, standard error; LS Mean, least-squares mean; CI, confidence interval, not adjusted for multiple comparisons.
aDifference (drug minus placebo) in least-squares mean change from baseline.

16 HOW SUPPLIED/STORAGE AND HANDLING

Focalin XR (dexmethylphenidate hydrochloride) extended-release capsules are available as follows:

100 Count

- 5 mg capsules (NDC 66758-235-01) light-blue, (imprinted “SDZ D5”) supplied in bottles of 100
- 10 mg capsules (NDC 66758-236-01) light caramel (imprinted “SDZ D10”) supplied in bottles of 100
- 15 mg capsules (NDC 66758-237-01) green (imprinted “SDZ D15”) supplied in bottles of 100
- 20 mg capsules (NDC 66758-238-01) white (imprinted “SDZ D20”) supplied in bottles of 100
- 25 mg capsules (NDC 66758-239-01) light-blue and white (imprinted “SDZ D25”) supplied in bottles of 100
- 30 mg capsules (NDC 66758-240-01) light caramel and white (imprinted “SDZ D30”) supplied in bottles of 100
- 35 mg capsules (NDC 66758-241-01) light-blue and light caramel (imprinted “SDZ D35”) supplied in bottles of 100
- 40 mg capsules (NDC 66758-242-01) green and white (imprinted “SDZ D40”) supplied in bottles of 100

30 Count

- 5 mg capsules (NDC 66758-235-31) light-blue, (imprinted “SDZ D5”) supplied in bottles of 30
- 10 mg capsules (NDC 66758-236-31) light caramel (imprinted “SDZ D10”) supplied in bottles of 30
- 15 mg capsules (NDC 66758-237-31) green (imprinted “SDZ D15”) supplied in bottles of 30
- 20 mg capsules (NDC 66758-238-31) white (imprinted “SDZ D20”) supplied in bottles of 30
- 25 mg capsules (NDC 66758-239-31) light-blue and white (imprinted “SDZ D25”) supplied in bottles of 30
- 30 mg capsules (NDC 66758-240-31) light caramel and white (imprinted “SDZ D30”) supplied in bottles of 30
- 35 mg capsules (NDC 66758-241-31) light-blue and light caramel (imprinted “SDZ D35”) supplied in bottles of 30
- 40 mg capsules (NDC 66758-242-31) green and white (imprinted “SDZ D40”) supplied in bottles of 30

Store at 20°C to 25°C (68°F to 77°F); excursions permitted between 15°C and 30°C (59°F and 86°F) [see USP Controlled Room Temperature].

Dispense in tight container (USP).

17 PATIENT COUNSELING INFORMATION

Advise patients to read the FDA-approved patient labeling (Medication Guide).

Abuse, Misuse, and Addiction

Educate patients and their families about the risks of abuse, misuse, and addiction of Focalin XR, which can lead to overdose and death, and proper disposal of any unused drug [see Warnings and Precautions (5.1), Drug Abuse and Dependence (9.2), Overdosage (10)]. Advise patients to store Focalin XR in a safe place, preferably locked, and instruct patients to not give Focalin XR to anyone else.

Risks to Patients with Serious Cardiac Disease

Advise patients that there are potential risks to patients with serious cardiac disease, including sudden death, with Focalin XR use. Instruct patients to contact a healthcare provider immediately if they develop symptoms, such as exertional chest pain, unexplained syncope, or other symptoms suggestive of cardiac disease [see Warnings and Precautions (5.2)].

Increased Blood Pressure and Heart Rate

Instruct patients that Focalin XR can cause elevations of their blood pressure and pulse rate [see Warnings and Precautions (5.3)].

Psychiatric Adverse Reactions

Advise patients that Focalin XR, at recommended doses, can cause psychotic or manic symptoms, even in patients without prior history of psychotic symptoms or mania [see Warnings and Precautions (5.4)].

Priapism

Advise patients of the possibility of painful or prolonged penile erections (priapism). Instruct them to seek immediate medical attention in the event of priapism [see Warnings and Precautions (5.5)].

Circulation Problems in Fingers and Toes (Peripheral Vasculopathy, Including Raynaud’s Phenomenon)

Instruct patients beginning treatment with Focalin XR about the risk of peripheral vasculopathy, including Raynaud’s phenomenon, and associated signs and symptoms: fingers or toes may feel numb, cool, painful, and/or may change color from pale, to blue, to red. Instruct patients to report to their physician any new numbness, pain, skin color change, or sensitivity to temperature in fingers or toes.

Instruct patients to call their physician immediately with any signs of unexplained wounds appearing on fingers or toes while taking Focalin XR. Further clinical evaluation (e.g., rheumatology referral) may be appropriate for certain patients [see Warnings and Precautions (5.6)].

Long-Term Suppression of Growth in Pediatric Patients

Advise patients that Focalin XR may cause slowing of growth and weight loss [see Warnings and Precautions (5.7)].

Increased Intraocular Pressure (IOP) and Glaucoma

Advise patients that IOP and glaucoma may occur during treatment with Focalin XR [see Warnings and Precautions (5.9)].

Motor and Verbal Tics, and Worsening of Tourette’s Syndrome

Advise patients that motor and verbal tics and worsening of Tourette’s Syndrome may occur during treatment with Focalin XR. Instruct patients to notify their healthcare provider if emergence of new tics or worsening of tics or Tourette’s syndrome occurs [see Warnings and Precautions (5.10)].

Pregnancy Registry

Advise patients that there is a pregnancy exposure registry that monitors pregnancy outcomes in patients exposed to ADHD medications, including Focalin XR, during pregnancy [see Use in Specific Populations (8.1)].

Manufactured by

Societal CDMO Gainesville, LLC

Gainesville, GA 30504 for

Sandoz Inc., Princeton, NJ 08540

6003692-01

MEDICATION GUIDE
FOCALIN XR® (foh-kuh-lin XR)
(dexmethylphenidate hydrochloride, USP)
extended-release capsules for oral use, CII

What is the most important information I should know about FOCALIN XR?

FOCALIN XR may cause serious side effects, including:

- Abuse, misuse, and addiction. FOCALIN XR has a high chance for abuse and misuse and may lead to substance use problems, including addiction. Misuse and abuse of FOCALIN XR, other methylphenidate containing medicines, and amphetamine containing medicines, can lead to overdose and death. The risk of overdose and death is increased with higher doses of FOCALIN XR or when it is used in ways that are not approved, such as snorting or injection.
  - Your healthcare provider should check you or your child’s risk for abuse, misuse, and addiction before starting treatment with FOCALIN XR and will monitor you or your child during treatment.
  - FOCALIN XR may lead to physical dependence after prolonged use, even if taken as directed by your healthcare provider.
  - Do not give FOCALIN XR to anyone else. See “What is FOCALIN XR?” for more information.
  - Keep FOCALIN XR in a safe place and properly dispose of any unused medicine. See “How should I store FOCALIN XR?” for more information.
  - Tell your healthcare provider if you or your child have ever abused or been dependent on alcohol, prescription medicines, or street drugs.
- Risks for people with serious heart disease. Sudden death has happened in people who have heart defects or other serious heart disease.

Your healthcare provider should check you or your child carefully for heart problems before starting FOCALIN XR. Tell your healthcare provider if you or your child have any heart problems, heart disease, or heart defects.

Call your healthcare provider or go to the nearest hospital emergency room right away if you or your child has any signs of heart problems, such as chest pain, shortness of breath, or fainting while taking FOCALIN XR.

- Increased blood pressure and heart rate. Your healthcare provider should check you or your child’s blood pressure and heart rate regularly during treatment with FOCALIN XR.
- Mental (psychiatric) problems:

All Patients

  - new or worse behavior and thought problems
  - new or worse bipolar illness
  - new psychotic symptoms (such as hearing voices, believing things that are not true, are suspicious) or new manic symptoms

Tell your healthcare provider about any mental problems you or your child have, or about a family history of suicide, bipolar illness, or depression.

Call your healthcare provider right away if you or your child have any new or worsening mental symptoms or problems while taking FOCALIN XR, especially seeing or hearing things that are not real, believing things that are not real, or are suspicious.

What is FOCALIN XR?

- FOCALIN XR is a central nervous system stimulant (CNS) prescription medicine. It is used for the treatment of Attention-Deficit Hyperactivity Disorder (ADHD). FOCALIN XR may help increase attention and decrease impulsiveness and hyperactivity in patients with ADHD.
- FOCALIN XR should be used as a part of a total treatment program for ADHD that may include counseling or other therapies.

Focalin XR is not recommended for use in children under 6 years of age with ADHD.

FOCALIN XR is a federally controlled substance (CII) because it contains dexmethylphenidate that can be a target for people who abuse prescription medicines or street drugs. Keep FOCALIN XR in a safe place to protect it from theft. Never give your FOCALIN XR to anyone else because it may cause death or harm them. Selling or giving away FOCALIN XR may harm others and is against the law.

Who should not take FOCALIN XR?
FOCALIN XR should not be taken if you or your child:

- are allergic to methylphenidate hydrochloride, or any of the ingredients in FOCALIN XR. See the end of this Medication Guide for a complete list of ingredients in FOCALIN XR.
- are taking or have taken within the past 14 days an anti-depression medicine called a monoamine oxidase inhibitor (MAOI).

FOCALIN XR may not be right for you or your child. Before starting FOCALIN XR, tell your or your child’s healthcare provider about all health conditions (or a family history of), including:

- heart problems, heart, disease, heart defects, or high blood pressure
- mental problems, including psychosis, mania, bipolar illness, or depression
- circulation problems in fingers or toes
- have eye problems, including increased pressure in your eye, glaucoma, or problems with your close-up vision (farsightedness)
- have or had repeated movements or sounds (tics) or Tourette’s syndrome, or have a family history of tics or Tourette’s syndrome.
- if you are pregnant or plan to become pregnant. It is not known if FOCALIN XR will harm your unborn baby.
  ∘ There is a pregnancy registry for females who are exposed to ADHD medications, including FOCALIN XR, during pregnancy. The purpose of the registry is to collect information about the health of females exposed to FOCALIN XR and their baby. If you or your child becomes pregnant during treatment with FOCALIN XR, talk to your healthcare provider about registering with the National Pregnancy Registry of ADHD medications at 1- 866-961-2388 or visit online at https://womensmentalhealth.org/adhd-medications/.
- if you are breastfeeding or plan to breastfeed. FOCALIN XR passes into your breast milk. Talk to your healthcare provider about the best way to feed the baby during treatment with FOCALIN XR.

Tell your healthcare provider about all of the medicines that you or your child takes, including prescription and over-the-counter medicines, vitamins, and herbal supplements. FOCALIN XR and some medicines may interact with each other and cause serious side effects. Sometimes the doses of other medicines will need to be adjusted while taking FOCALIN XR.

Your healthcare provider will decide whether FOCALIN XR can be taken with other medicines.

Especially tell your healthcare provider if you or your child takes:

- anti-depression medicines, including MAOIs
- blood pressure medicines (anti-hypertensive)

Know the medicines that you or your child takes. Keep a list of your medicines with you to show your healthcare

provider and pharmacist.

- You should not take FOCALIN XR on the day of your operation if a certain type of anesthetic is used. This is because there is a chance of a sudden rise in blood pressure and heart rate during the operation.

Do not start any new medicine while taking FOCALIN XR without talking to your healthcare provider first.

How should FOCALIN XR be taken?

- Take FOCALIN XR exactly as prescribed. Your healthcare provider may adjust the dose until it is right for you or your child.
- Take FOCALIN XR once each day in the morning. FOCALIN XR is an extended-release capsule.
- FOCALIN XR can be taken with or without food. Taking FOCALIN XR with food may slow the time it takes for the medicine to start working.
- Swallow FOCALIN XR capsules whole with water or other liquids. Do not chew, crush, or divide the capsules or the beads in the capsule. If you or your child cannot swallow the capsule, open it and sprinkle the small beads of medicine over a spoonful of applesauce and swallow it right away without chewing.
- Your healthcare provider may do regular checks of the blood, heart, and blood pressure while taking FOCALIN XR.
- Children should have their height and weight checked often while taking FOCALIN XR. FOCALIN XR treatment may be stopped if a problem is found during these check-ups.

If you or your child take too much FOCALIN XR, call your healthcare provider or Poison Help line at 1-800-222-1222 or go to the nearest hospital emergency room right away.

What are the possible side effects of FOCALIN XR?
FOCALIN XR may cause serious side effects, including:

- see “What is the most important information I should know about FOCALIN XR?” for information on reported heart and mental problems.
- painful and prolonged erections (priapism) have occurred with methylphenidate. If you or your child develops priapism, seek medical help right away. Because of the potential for lasting damage, priapism should be evaluated by a healthcare provider immediately.
- circulation problems in fingers and toes (peripheral vasculopathy, including Raynaud’s phenomenon):
  - fingers or toes may feel numb, cool, painful
  - fingers or toes may change color from pale, to blue, to red

Tell your healthcare provider if you or your child have, numbness, pain, skin color change, or sensitivity to temperature in the fingers or toes.

- Call your healthcare provider right away if you have or your child has any signs of unexplained wounds appearing on fingers or toes while taking FOCALIN XR.
- Slowing of growth (height and weight) in children. Children should have their height and weight checked often during treatment with FOCALIN XR. FOCALIN XR treatment may be stopped if your child is not growing or gaining weight.
- Eye problems (increased pressure in the eye and glaucoma). Call your healthcare provider right away if you or your child develop changes in your vision or eye pain, swelling, or redness.
- New or worsening tics or worsening Tourette’s syndrome. Tell your healthcare provider if you or your child get any new or worsening tics or worsening Tourette’s syndrome during treatment with FOCALIN XR.

Common side effects include:
Children (6–17 years)

• dyspepsia

• decreased appetite

• headache

• anxiety

Adults

• dry mouth

• dyspepsia

• headache

• anxiety

• pharyngolaryngeal pain

Call your doctor for medical advice about side effects. You may report side effects to FDA at 1-800-FDA-1088.

How should I store FOCALIN XR?

- Store FOCALIN XR in a safe place and in a tightly closed container at room temperature between 68°F to 77°F (20°C to 25°C).
- Dispose of remaining, unused, or expired FOCALIN XR by a medicine take-back program at a U.S. Drug Enforcement Administration (DEA) authorized collection site. If no take-back program or DEA authorized collector is available, mix FOCALIN XR with an undesirable, nontoxic substance such as dirt, cat litter, or used coffee grounds to make it less appealing to children and pets. Place the mixture in a container, such as a sealed plastic bag and throw away FOCALIN XR in the household trash. Visit www.fda.gov/drugdisposal for additional information on disposal of unused medicine.
- Keep FOCALIN XR and all medicines out of the reach of children.

General information about the safe and effective use of FOCALIN XR.
Medicines are sometimes prescribed for purposes other than those listed in a Medication Guide. You can ask your pharmacist or healthcare provider for information about FOCALIN XR that is written for healthcare professionals. Do not use FOCALIN XR for a condition for which it was not prescribed. Do not give FOCALIN XR to other people, even if they have the same symptoms that you have. It may harm them and it is against the law.

What are the ingredients in FOCALIN XR?
Active ingredient: dexmethylphenidate hydrochloride

Inactive ingredients: ammonio methacrylate copolymer, gelatin, methacrylic acid copolymer, polyethylene glycol, sugar spheres, talc, titanium dioxide, and triethyl citrate.
Each strength capsule also contains colorant ingredients in the capsule

shell as follows:

• 5 mg: E132 FD&C Blue No. 2

• 10 mg: FDA/E172 iron oxide yellow

• 15 mg: FD&C Blue No. 2, FDA/E172 iron oxide yellow

• 20 mg: contains no colorants

• 25 mg: E132 FD&C Blue No. 2

• 30 mg: FDA/E172 iron oxide yellow

• 35 mg: E132 FD&C Blue No. 2, FDA/E172 iron oxide yellow

• 40 mg: E132 FD&C Blue No. 2, FDA/E172 iron oxide yellow

Manufactured by

Societal CDMO Gainesville, LLC

Gainesville, GA 30504 for

Sandoz Inc., Princeton, NJ 08540

For additional medication guide please go to www.us.sandoz.com or call 1-800-525-8747.

This Medication Guide has been approved by the U.S. Food and Drug Administration. Revised: 09/2025

6003692-01

PRINCIPAL DISPLAY PANEL

NDC 66758-235-01 Rx only

Focalin XR®

(dexmethylphenidate HCl)

extended-release capsules

5 mg

100 capsules

Dispense with Medication
Guide attached or provided
separately.

SANDOZ

PRINCIPAL DISPLAY PANEL

NDC 66758-236-01 Rx only

Focalin XR®

(dexmethylphenidate HCl)

extended-release capsules

10 mg

100 capsules

Dispense with Medication
Guide attached or provided
separately.

SANDOZ

PRINCIPAL DISPLAY PANEL

NDC 66758-237-01 Rx only

Focalin XR®

(dexmethylphenidate HCl)

extended-release capsules

15 mg

100 capsules

Dispense with Medication
Guide attached or provided
separately.

SANDOZ

PRINCIPAL DISPLAY PANEL

NDC 66758-238-01 Rx only

Focalin XR®

(dexmethylphenidate HCl)

extended-release capsules

20 mg

100 capsules

Dispense with Medication
Guide attached or provided
separately.

SANDOZ

PRINCIPAL DISPLAY PANEL

NDC 66758-239-01 Rx only

Focalin XR®

(dexmethylphenidate HCl)

extended-release capsules

25 mg

100 capsules

Dispense in tight container (USP).

Dispense with Medication Guide
attached or provided separately.

SANDOZ

PRINCIPAL DISPLAY PANEL

NDC 66758-240-01 Rx only

Focalin XR®

(dexmethylphenidate HCl)

extended-release capsules

30 mg

100 capsules

Dispense in tight container (USP).

Dispense with
Medication Guide attached
or provided separately.

SANDOZ

PRINCIPAL DISPLAY PANEL

NDC 66758-241-01 Rx only

Focalin XR®

(dexmethylphenidate HCl)

extended-release capsules

35 mg

100 capsules

Dispense in tight container (USP).

Dispense with
Medication Guide attached
or provided separately.

SANDOZ

PRINCIPAL DISPLAY PANEL

NDC 66758-242-01 Rx only

Focalin XR®

(dexmethylphenidate HCl)

extended-release capsules

40 mg

100 capsules

Dispense in tight container (USP).

Dispense with
Medication Guide attached
or provided separately.

SANDOZ

PACKAGE/LABEL PRINCIPAL DISPLAY PANEL

NDC 66758-235-31 Rx only

Focalin XR®

(dexmethylphenidate HCl)

extended-release capsules

5 mg

Dispense with Medication Guide

attached or provided separately.

30 capsules

SANDOZ

PACKAGE/LABEL PRINCIPAL DISPLAY PANEL

NDC 66758-236-31 Rx only

Focalin XR®

(dexmethylphenidate HCl)

extended-release capsules

10 mg

Dispense with Medication Guide

attached or provided separately.

30 capsules

SANDOZ

PACKAGE/LABEL PRINCIPAL DISPLAY PANEL

NDC 66758-237-31 Rx only

Focalin XR®

(dexmethylphenidate HCl)

extended-release capsules

15 mg

Dispense with Medication Guide

attached or provided separately.

30 capsules

SANDOZ

PACKAGE/LABEL PRINCIPAL DISPLAY PANEL

NDC 66758-238-31 Rx only

Focalin XR®

(dexmethylphenidate HCl)

extended-release capsules

20 mg

Dispense with Medication Guide

attached or provided separately.

30 capsules

SANDOZ

PACKAGE/LABEL PRINCIPAL DISPLAY PANEL

NDC 66758-239-31 Rx only

Focalin XR®

(dexmethylphenidate HCl)

extended-release capsules

25 mg

Dispense with Medication Guide

attached or provided separately.

30 capsules

SANDOZ

PACKAGE/LABEL PRINCIPAL DISPLAY PANEL

NDC 66758-240-31 Rx only

Focalin XR®

(dexmethylphenidate HCl)

extended-release capsules

30 mg

Dispense with Medication Guide

attached or provided separately.

30 capsules

SANDOZ

PACKAGE/LABEL PRINCIPAL DISPLAY PANEL

NDC 66758-241-31 Rx only

Focalin XR®

(dexmethylphenidate HCl)

extended-release capsules

35 mg

Dispense with Medication Guide

attached or provided separately.

30 capsules

SANDOZ

PACKAGE/LABEL PRINCIPAL DISPLAY PANEL

NDC 66758-242-31 Rx only

Focalin XR®

(dexmethylphenidate HCl)

extended-release capsules

40 mg

Dispense with Medication Guide

attached or provided separately.

30 capsules

SANDOZ